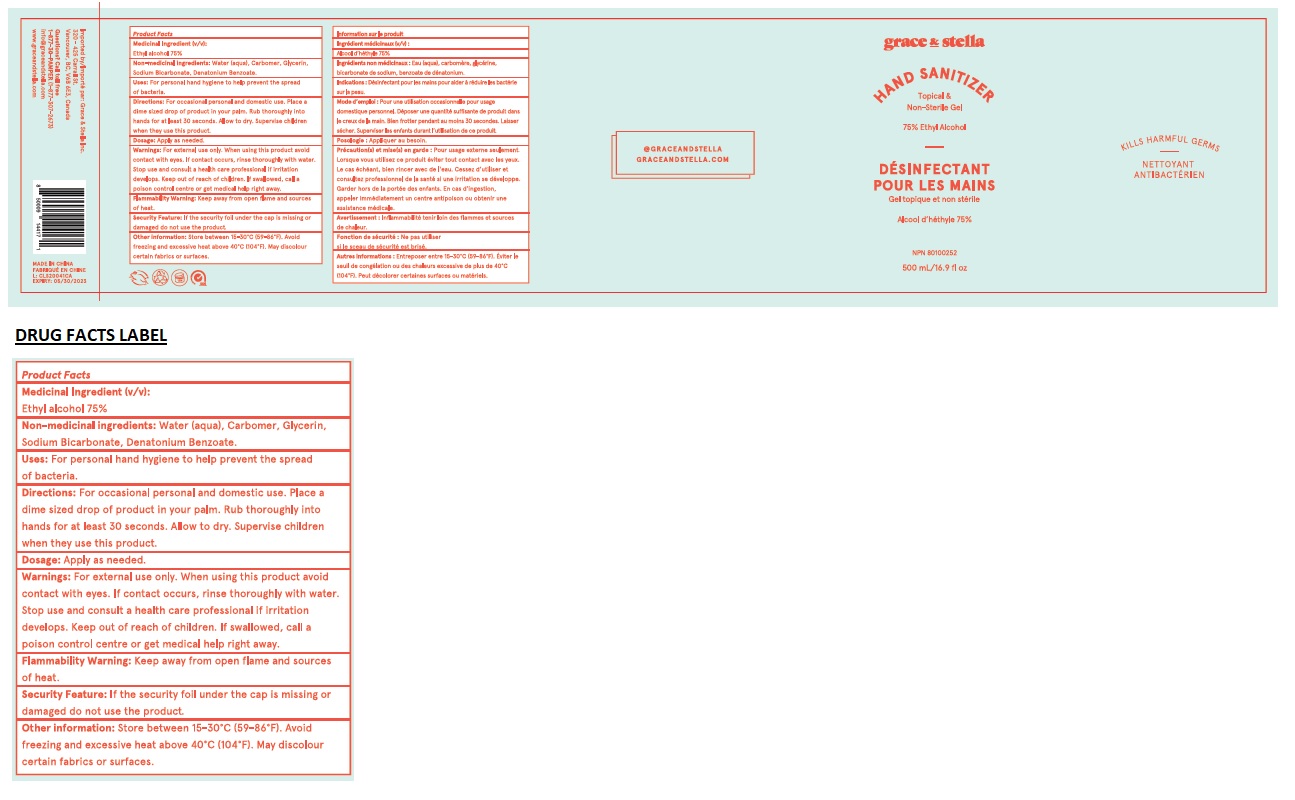 DRUG LABEL: GRACE AND STELLA HAND SANITIZER
NDC: 76851-102 | Form: GEL
Manufacturer: Grace & Stella Inc
Category: otc | Type: HUMAN OTC DRUG LABEL
Date: 20200506

ACTIVE INGREDIENTS: ALCOHOL 75 mL/100 mL
INACTIVE INGREDIENTS: WATER; CARBOMER HOMOPOLYMER, UNSPECIFIED TYPE; GLYCERIN; SODIUM BICARBONATE; DENATONIUM BENZOATE

grace & stella HAND SANITIZER

Medicinal Ingredient (v/v):

Ethyl alcohol 75%

Purpose

Antiseptic

INACTIVE INGREDIENT

Non-medicinal ingredients: Water (aqua), Carbomer, Glycerin, Sodium Bicarbonate, Denatonium Benzoate.

INDICATIONS AND USAGE

Uses: For personal hand hygiene to help prevent the spread of bacteria.

DOSAGE AND ADMINISTRATION

Directions: For occasional personal and domestic use. Place a dime sized drop of product in your palm. Rub thoroughly into hands for at least 30 seconds. Allow to dry. Supervise children when they use this product.

Dosage: Apply as needed.

Warnings: For external use only.

When using this product avoid contact with eyes. If contact occurs, rinse thoroughly with water.

Stop use and consult a health care professional if irritation develops.

Flammability Warning: Keep away from open flame and sources of heat.

Security Feature: If the security foil under the cap is missing or damaged do not use the product.

Keep out of reach of children. If swallowed, call a poison control centre or get medical help right away.

Other information: Store between 15-30°C (59-86°F). Avoid freezing and excessive heat above 40°C (104°F). May discolour certain fabrics or surfaces.

Topical & Non-Sterile Gel

75% Ethyl Alcohol

KILLS HARMFUL GERMS

Imported by: Grace & Stella Inc.

320 - 425 Carrall St.

Vancouver, BC, V6B 6E3, Canada

Questions?? Call toll free

1-877-30-PAMPER (1-877-307-2673)

info@graceandstella.com

www.graceandstella.com

MADE IN CHINA

@GRACEANDSTELLA

GRACEANDSTELLA.COM